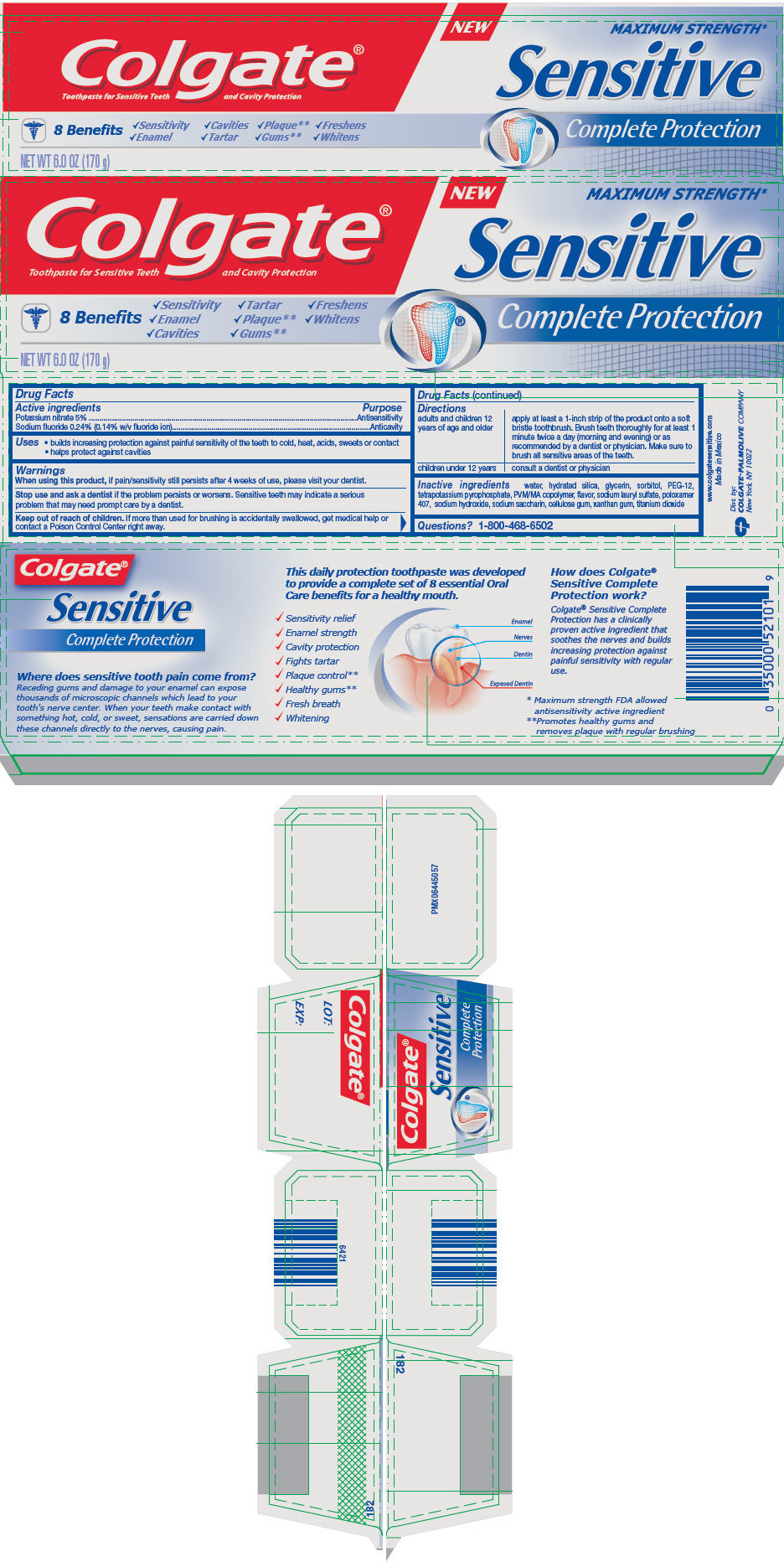 DRUG LABEL: Colgate Sensitive Complete Protection
NDC: 35000-965 | Form: PASTE, DENTIFRICE
Manufacturer: Colgate-Palmolive Company
Category: otc | Type: HUMAN OTC DRUG LABEL
Date: 20191218

ACTIVE INGREDIENTS: SODIUM FLUORIDE 2.4 mg/1 g; POTASSIUM NITRATE 50 mg/1 g
INACTIVE INGREDIENTS: WATER 189.046 mg/1 g; HYDRATED SILICA; GLYCERIN; SORBITOL; POLYETHYLENE GLYCOL 600; POTASSIUM PYROPHOSPHATE; BUTYL ESTER OF METHYL VINYL ETHER/MALEIC ANHYDRIDE COPOLYMER (125000 MW); SODIUM LAURYL SULFATE; POLOXAMER 407; SODIUM HYDROXIDE; SACCHARIN SODIUM; CARBOXYMETHYLCELLULOSE SODIUM, UNSPECIFIED; XANTHAN GUM; TITANIUM DIOXIDE

Colgate® Sensitive Complete Protection Toothpaste

Drug Facts

ACTIVE INGREDIENT

Active ingredients | Purpose
Potassium nitrate 5% | Antisensitivity
Sodium fluoride 0.24% (0.14% w/v fluoride ion) | Anticavity

Uses

- builds increasing protection against painful sensitivity of the teeth to cold, heat, acids, sweets or contact
- helps protect against cavities

Warnings

When using this product, if pain/sensitivity still persists after 4 weeks of use, please visit your dentist.

Stop use and ask a dentist if the problem persists or worsens. Sensitive teeth may indicate a serious problem that may need prompt care by a dentist.

Keep out of reach of children. If more than used for brushing is accidentally swallowed, get medical help or contact a Poison Control Center right away.

Directions

adults and children 12 years of age and older | apply at least a 1-inch strip of the product onto a soft bristle toothbrush. Brush teeth thoroughly for at least 1 minute twice a day (morning and evening) or as recommended by a dentist or physician. Make sure to brush all sensitive areas of the teeth.
children under 12 years | consult a dentist or physician

Inactive ingredients

water, hydrated silica, glycerin, sorbitol, PEG-12, tetrapotassium pyrophosphate, PVM/MA copolymer, flavor, sodium lauryl sulfate, poloxamer 407, sodium hydroxide, sodium saccharin, cellulose gum, xanthan gum, titanium dioxide

Questions?

1-800-468-6502

Dist. by:
COLGATE-PALMOLIVE COMPANY
New York, NY 10022

PRINCIPAL DISPLAY PANEL - 170 g Tube Carton

Colgate®
Toothpaste for Sensitive Teeth and Cavity Protection

8 Benefits

✓Sensitivity ✓Tartar ✓Freshens
✓Enamel ✓Plaque** ✓Whitens
✓Cavities ✓Gums**

NET WT 6.0 OZ (170 g)

NEW
MAXIMUM STRENGTH*

Sensitive

Complete Protection